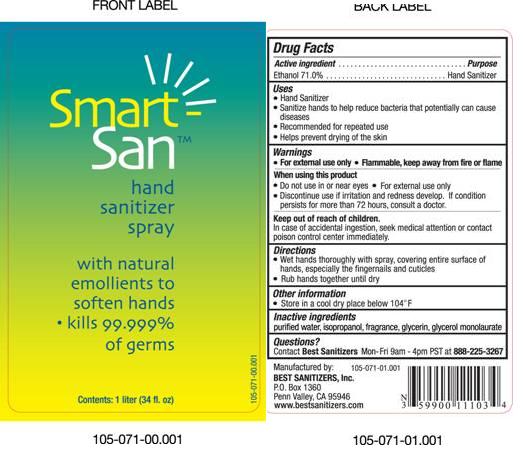 DRUG LABEL: Smart San Hand Sanitizer Spray
NDC: 59900-111 | Form: LIQUID
Manufacturer: Best Sanitizers, Inc
Category: otc | Type: HUMAN OTC DRUG LABEL
Date: 20100305

ACTIVE INGREDIENTS: Ethanol 710 g/1000 mL

Drug Facts

Active Ingredient

Ethanol 71.0%

Purpose

Hand Sanitizer

Uses

- Hand Sanitizer
- Sanitize hands to help reduce bacteria that potentially can cause disease
- Recommended for repeated use
- Helps prevent drying of the skin

Warnings

- For external use only
- Flammable, keep away from fire or flame

When Using this product

- Do not use in or near eyes.
- For external use only
- Discontinue use if irritation and redness develop If condition persists for more that 72 hours, consult a doctor.

Keep out of reach of children

In case of accidental ingestion seek medical attention or contact a poison center immediately.

Directions

- Wet hands thoroughly with spray, covering entire surface of hands, especially the fingertips and cuticles
- Rub hands together until dry.

Other Information

- Store in a cool dry place below 104° F

Inactive ingredients

purified water, isopropanol, fragrance, glycerin, glycerol monolaurate

Questions?

Contact Best Sanitizers Mon-Fri 9am - 4pm PST at 888-225-3267

Principal Display Panel

NDC 59900-111-02

NDC 59900-111-03

NDC 59900-111-04

NDC 59900-111-05

NDC 59900-111-06

Smart San™ Hand Sanitizer Spray